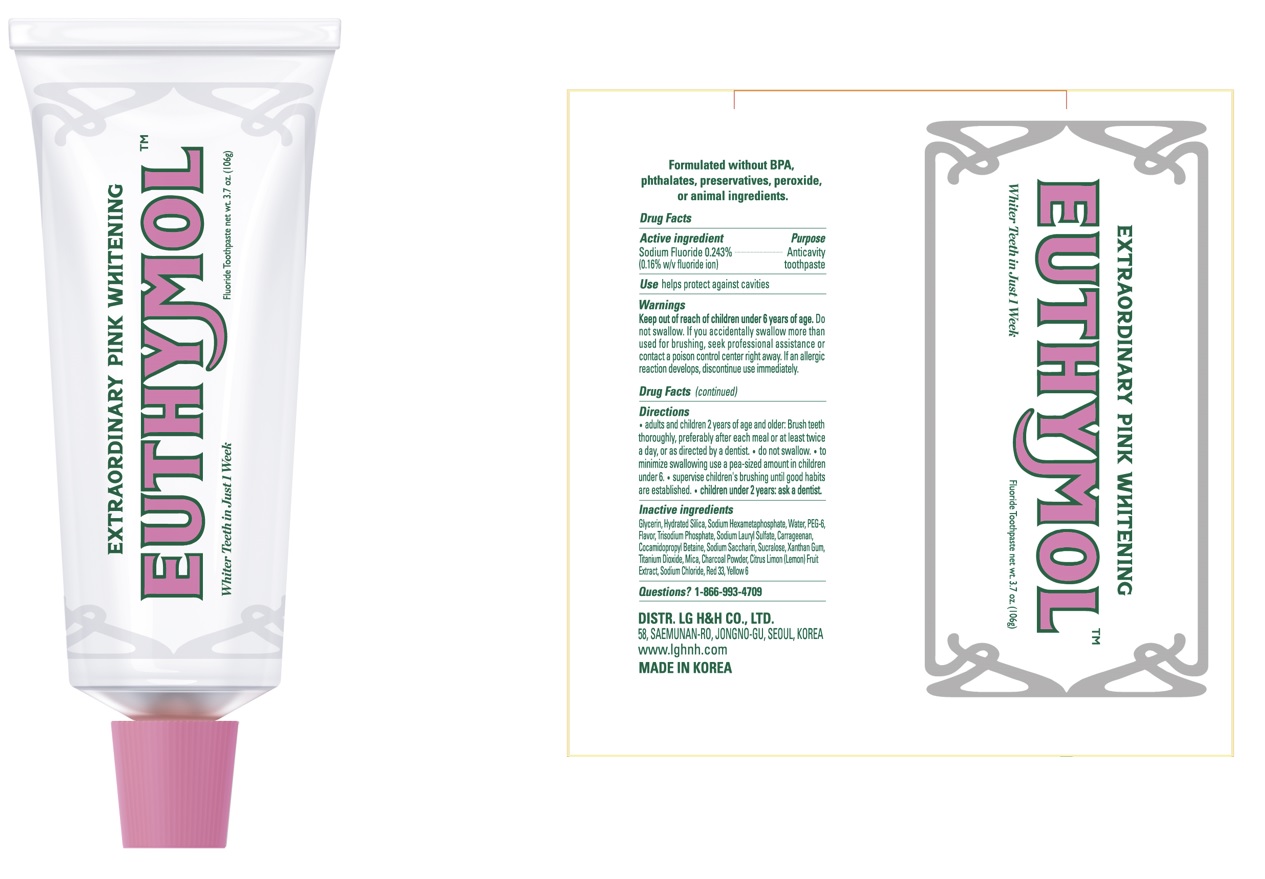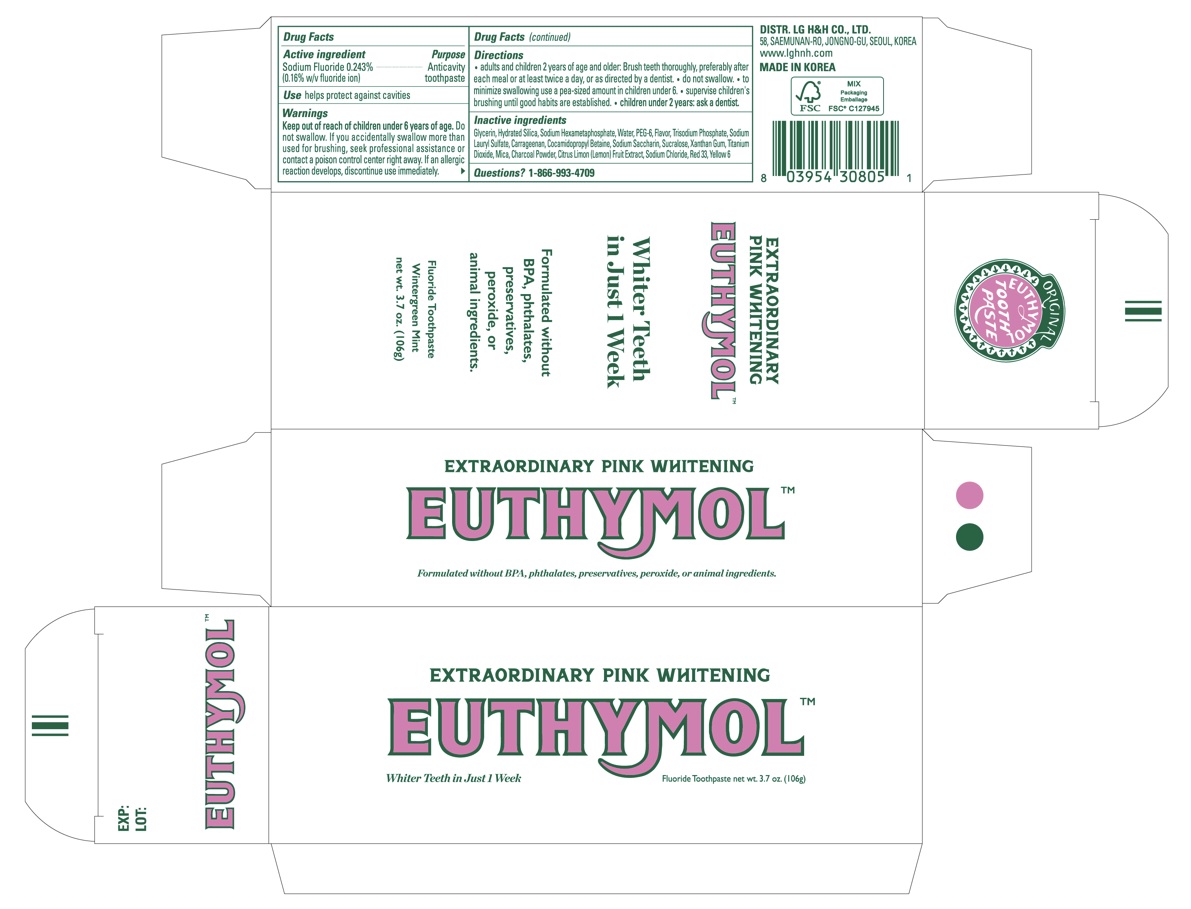 DRUG LABEL: EUTHYMOL Extraordinary Pink Whitening
NDC: 43136-501 | Form: PASTE, DENTIFRICE
Manufacturer: Tai Guk Pharm. Co., Ltd.
Category: otc | Type: HUMAN OTC DRUG LABEL
Date: 20250101

ACTIVE INGREDIENTS: SODIUM FLUORIDE 1.6 mg/1 g
INACTIVE INGREDIENTS: POLYETHYLENE GLYCOL 300; SODIUM POLYMETAPHOSPHATE; CARRAGEENAN; GLYCERIN; WATER; COCAMIDOPROPYL BETAINE; SODIUM PHOSPHATE, TRIBASIC, ANHYDROUS; SODIUM LAURYL SULFATE; XANTHAN GUM; SACCHARIN SODIUM; SUCRALOSE; TITANIUM DIOXIDE; CITRUS LIMON FRUIT OIL; SODIUM CHLORIDE; HYDRATED SILICA; MICA; ACTIVATED CHARCOAL

EUTHYMOL Extraordinary Pink Whitening Toothpaste (106g)

Drug Facts

Active Ingredient

Sodium Fluoride 0.243% (0.16% w/v fluoride ion)

Purpose

Anticavity toopaste

Use

helps protect against cavities

Warnings

Keep out of reach of children under 6 years of age.Do not swallow. If you accidentally swallow more than used for brushing, seek professional assistance or contact a poison control center right away. If an allergic reaction develops, discontinue use immediately.

Directions

- adults and children 2 years of age and and older: Brush teeth thoroughly, preferably after each meal or at least twice a day, or as directed by a dentist.
- Do not swallow.
- to minimize swallowing use a pea-sized amount in children under 6.
- Supervise children's brushing until good habits are established.
- Children under 2 years: ask a dentist.

Inactive Ingredients

GLYCERIN, HYDRATED SILICA, SODIUM HEXAMETAPHOSPHATE, WATER, PEG-6, FLAVOR, TRISODIUM PHOSPHATE, SODIUM LAURYL SULFATE, CARRAGEENAN, COCAMIDOPROPYL BETAINE, SODIUM SACCHARIN, SUCRALOSE, XANTHAN GUM, TITANIUM DIOXIDE, MICA, CHARCOAL POWDER, CITRUS LIMON(LEMON) FRUIT EXTRACT, SODIUM CHLORIDE

Questions?

1-866-993-4709

Principal Display Panel - 106 g Tube Carton

EXTRAORDINARY

PINK WHITENING

EUTHYMOL

Whiter Teeth in Just 1 Week
Formulated without BPA, phthalates, preservatives, peroxide, or animal ingredients.
Fluoride Toothpaste

Wintergreen Mint

net wt. 3.7 oz (106 g)

DIST. LG H&H CO., LTD.
58, SAEMUNAN-RO, JONGNO-GU, SEOUL, KOREA
www.lghnh.com
MADE IN KOREA